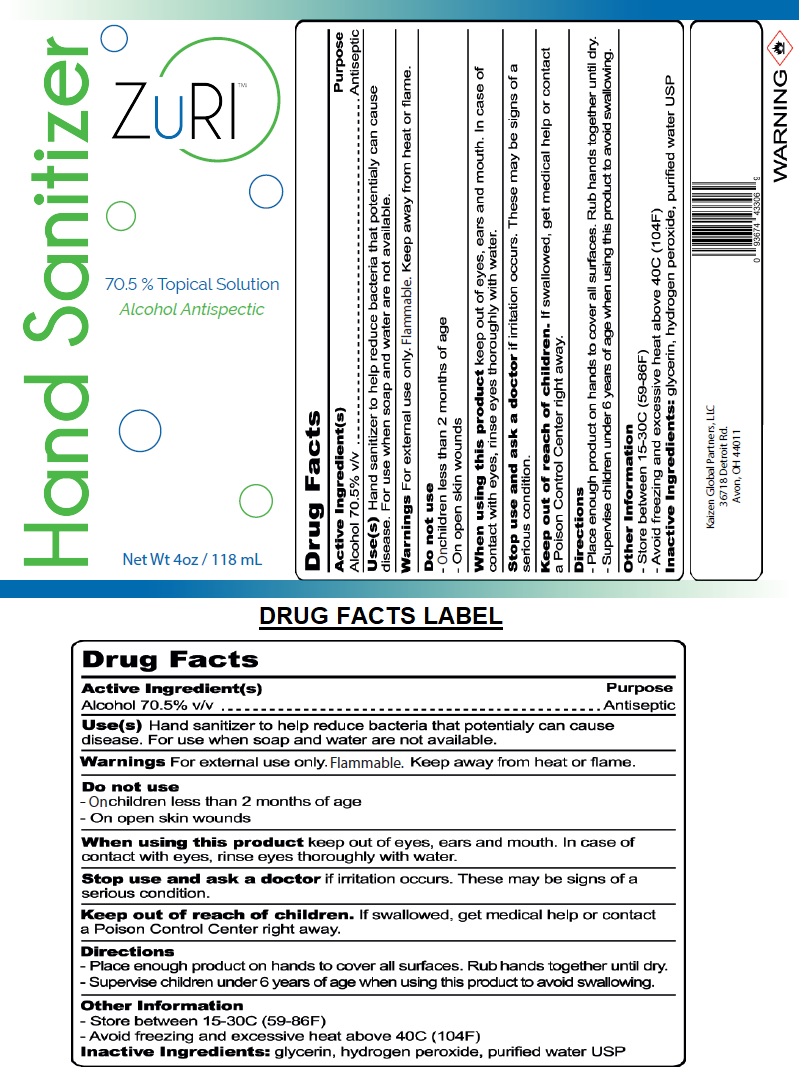 DRUG LABEL: ZuRI 70.5% Topical Solution Hand Sanitizer
NDC: 80347-070 | Form: GEL
Manufacturer: Kaizen Global Partners Llc
Category: otc | Type: HUMAN OTC DRUG LABEL
Date: 20200924

ACTIVE INGREDIENTS: ALCOHOL 70.5 mL/100 mL
INACTIVE INGREDIENTS: GLYCERIN; HYDROGEN PEROXIDE; WATER

ZuRI™ Hand Sanitizer

Active Ingredient(s)

Alcohol 70.5% v/v

Purpose

Antiseptic

INDICATIONS AND USAGE

Uses(s) Hand sanitizer to help reduce bacteria that potentially can cause disease. For use when soap and water are not available.

WARNINGS

Warnings For external use only. Flammable. Keep away from heat or flame.

Do not use

- On children less than 2 months of age
- On open skin wounds

When using this product keep out of eyes, ears and mouth. In case of contact with eyes, rinse eyes thoroughly with water.

Stop use and ask a doctor if irritation occurs. These may be signs of a serious condition.

Keep out of reach of children. If swallowed, get medical help or contact a Poison Control Center right away.

Directions

- Place enough product on hands to cover all surfaces. Rub hands together until dry.
- Supervise children under 6 years of age when using this product to avoid swallowing.

Other Information

- Store between 15-30C (59-86F)
- Avoid freezing and excessive heat above 40C (104F)

Inactive Ingredients: glycerin, hydrogen peroxide, purified water USP

70.5% Topical Solution

Alcohol Antiseptic

Kaizen Global Partners, LLC

36718 Detroit Rd.

Avon, OH 44011